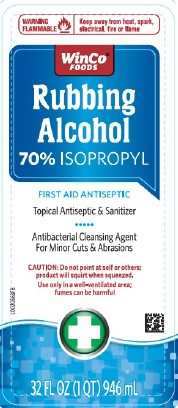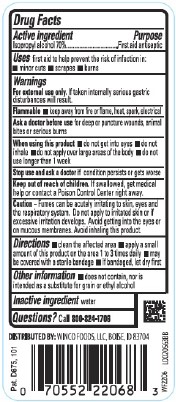 DRUG LABEL: 70% Isopropyl Rubbing Alcohol
NDC: 67091-100 | Form: SOLUTION
Manufacturer: WinCo Foods, LLC
Category: otc | Type: HUMAN OTC DRUG LABEL
Date: 20260212

ACTIVE INGREDIENTS: ISOPROPYL ALCOHOL 70 mL/100 mL
INACTIVE INGREDIENTS: WATER

WinCo 810.003/810AA
70% Isopropyl Rubbing Alcohol

Active ingredient

Isopropyl Alcohol 70%

Purpose

First Aid Antiseptic

Use

first aid to help prevent the risk of infection in:

- Minor cuts
- Scrapes
- Burns

Warnings

For external use only. If taken interanlly serious gastic disturbances will result.

Flammable Keep away from fire or flame, heat, spark, electrical

Ask a doctor before use if you have

deep or puncture wounds, animal bites or serious burns

When using this product

- do not get into eyes
- do not inhale
- do not apply over large areas of the body
- do not use longer than 1 week

Stop use and ask a doctor if

Condition persists or gets worse

Keep out of reach of children.

If swallowed, get medical help or contact a Poison Control Center right away.

Caution

Fumes can be acutely irritating to skin, eyes and the respiratory system. Do not apply to irritated skin or if excessive irritation develops. Aviod getting into the eyes or mucous membranes. Avoid inhaling this product.

Directions

- Clean the affected area
- Apply a small amount of this product on the affected area 1 to 3 times daily
- May be covered with a sterile bandage
- If bandaged, let dry first

Other information

- Does not contain, nor is intended as a substitute for grain or ethyl alcohol

Inactive ingredient

water

Questions?

Call 800-824-1706

ADVERSE REACTION

DISTRIBUTED BY: WINCO FOODS, LLC, BOISE, ID 83704

Pat. D675, 101

principal display panel

WARNING FLAMMABLE - Keep away from heat, spark, electrical, fire or flame

WinCo®Foods

Rubbing Alcohol

70% Isopropyl

FIRST AID ANTISEPTIC

Topical atiseptic and sanitizer

Antibacterial cleansing agent for minor cuts and abrasions

CAUTION: Do not point at self or others; product will squirt when squeezed.

Use only in well-ventilated area; fumes can be harmful.

32 FL OZ (1 QT) 946 mL